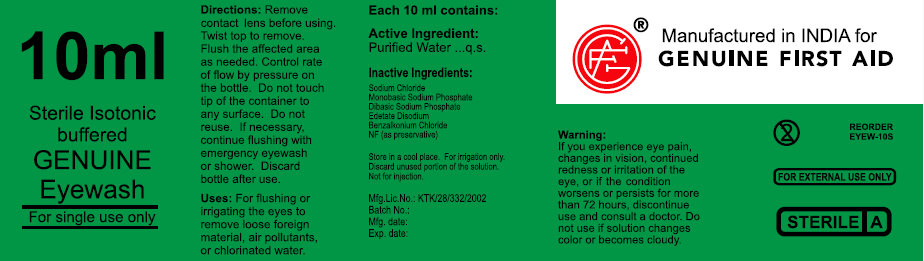 DRUG LABEL: Sterile Isotonic Buffered Genuine Eyewash
NDC: 52124-0005 | Form: LIQUID
Manufacturer: Genuine First Aid
Category: otc | Type: HUMAN OTC DRUG LABEL
Date: 20100712

ACTIVE INGREDIENTS: WATER 98.16 mL/100 mL
INACTIVE INGREDIENTS: SODIUM CHLORIDE; SODIUM PHOSPHATE, MONOBASIC; SODIUM PHOSPHATE, DIBASIC; EDETATE DISODIUM; BENZALKONIUM CHLORIDE

Sterile Isotonic Buffered Genuine Eyewash

Active Ingredient:

Purified Water USP...q.s.

Inactive Ingredients:

Sodium Chloride USP 44mg

Monobasic Sodium Phosphate USP 18mg

Sodium Phosphate Dibasic USP 111mg
Edetate Disodium USP 10mg
Benzalkonium Chloride 0.5mg
NF (as preservative)

STORAGE AND HANDLING

Store in a cool place. For irrigation only.

Discard unused portion of the solution.

Not for injection.

Warning:

If you experience eye pain, changes in vision, continued redness or irritation of the eye,

or if the condition worsens or persists for more than 72 hours, discontinue use and consult a doctor.

Do not use if solution changes color or becomes cloudy.

Directions
Remove contacts before using.
Twist top to remove.
Flush the affected area as needed. Control
Rate of flow by pressure on the bottle. Do not touch
tip of the container to any surface. Do not reuse.
If necessary continue flushing with emergency eyewash or shower.
Discard bottle after use.

Uses:
For flushing or irrigating the eyes to
remove loose foreign material, air pollutants,
or chlorinated water.

DESCRIPTION

Code No.: GUJ/DRUG/G/1080

Batch No.:

Mfg Date:

Exp: Date:

PACKAGE LABEL

10ml

Sterile Isotonic Buffered Genuine

Eyewash

For single use only